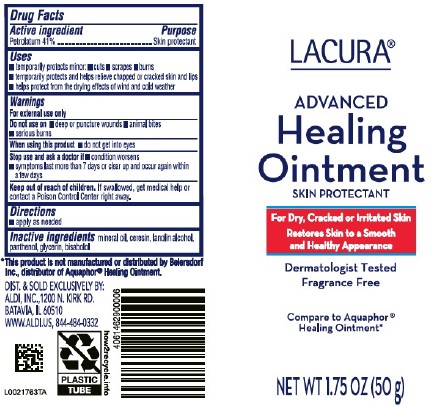 DRUG LABEL: Advanced Healing
NDC: 64024-247 | Form: OINTMENT
Manufacturer: Aldi, Inc
Category: otc | Type: HUMAN OTC DRUG LABEL
Date: 20260129

ACTIVE INGREDIENTS: PETROLATUM 410 mg/1 g
INACTIVE INGREDIENTS: MINERAL OIL; CERESIN; LANOLIN ALCOHOLS; PANTHENOL; GLYCERIN; LEVOMENOL

Lacura 247.000/247AA-AC
Healing Ointment for Dry and Cracked Skin

Active Ingredient

Petrolatum 41%

Purpose

Skin protectant

Uses

- temporarily protects minor:
- cuts
- scrapes
- burns
- temporarily protects and helps relieve chapped or cracked skin and lips
- helps protect from the drying effects of wind and cold weather

Warnings

For external use only

Do not use on

- deep or puncture wounds
- animal bites
- serious burns

When using this product

- do not get into eyes

Stop use and ask a doctor

- condition worsens
- symptoms last more than 7 days or clear up and occur again within a few days

Keep out of reach of children.

If swallowed, get medical help or contact a Poison Control Center right away.

Directions

- apply as needed

Inactive ingredients

mineral oil, ceresin, lanolin alcohol, panthenol, glycerin, bisabolol

Disclaimer

*This product is not manufactured or distributed by Beiersdorf Inc, distributor of Aquaphor® Healing Ointment.

Adverse reaction

DIST. & SOLD EXCLUSIVELY BY:

ALDI, INC., 1200 N. KIRK RD.

BATAVIA, IL 60510

WWW.ALDI.US, 844-484-0332

PLASTIC TUBE

how2recycle.info

Principal panel display

LACURA®

ADVANCED

Healing Ointment

SKIN PROTECTANT

For Dry, Cracked or Irritated Skin

Restores Skin to a Smooth and Healthy Appearance

Dermatologist Tested

Fragrance Free

Compare to Aquaphor®Healing Ointment*

NET WT 1.75 OZ (50 g)